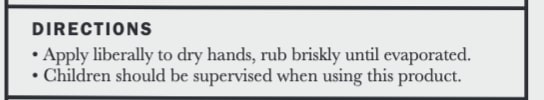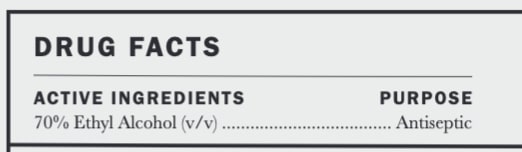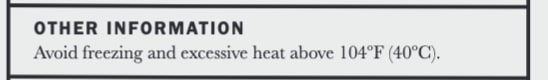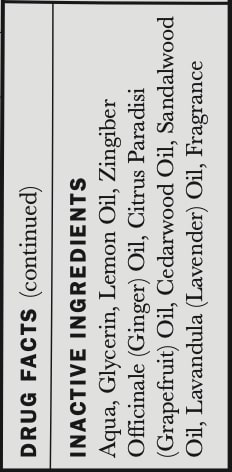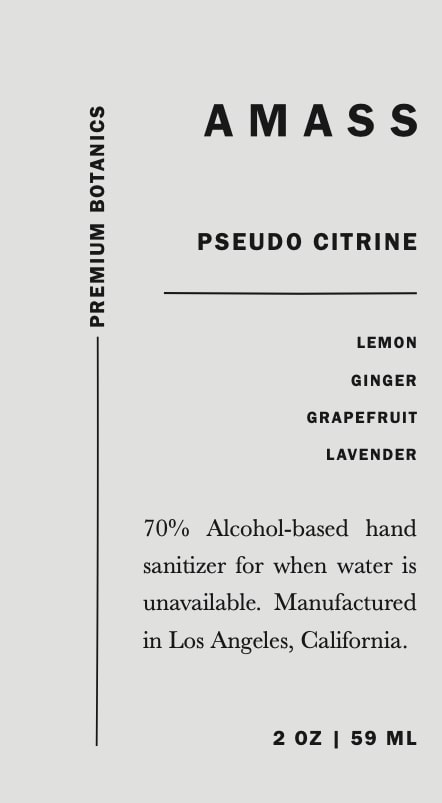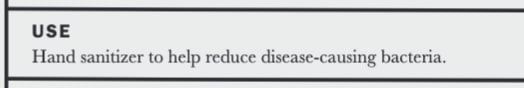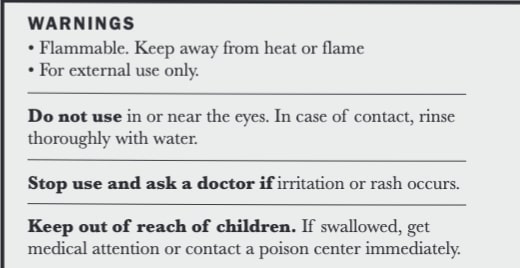 DRUG LABEL: AMASS Pseudo Citrine Sanitizer Liquid
NDC: 77419-5000 | Form: LIQUID
Manufacturer: AMASS Brands, Inc
Category: otc | Type: HUMAN OTC DRUG LABEL
Date: 20221031

ACTIVE INGREDIENTS: ALCOHOL 43.66 mL/59 mL
INACTIVE INGREDIENTS: WATER; GLYCEROL FORMAL; CEDRUS ATLANTICA BARK OIL; SANDALWOOD OIL; LAVENDER OIL; GINGER OIL; BENZYL BENZOATE; LEMON OIL; GRAPEFRUIT OIL; METHYL DIHYDROJASMONATE (SYNTHETIC); LIMONENE, (+)-

Active Ingredients ......... Purpose
70% Ethyl Alcohol (v/v)........ Antiseptic

Do not use in or near the eyes. In case of contact, rinse thoroughly with water.

Keep out of reach of children. If swallowed, get medical attention or contact a poison center immediately.

USE
Hand sanitizer to help reduce disease-causing bacteria

Stop use and ask a doctor if irriation or rash occurs.

Directions
Apply liberally to dry hands, rub briskly until evaporated
Children should be supervised when using this product

OTHER INFORMATION
Avoid freezing and excessive heat above 104F (40C)

WARNINGS
Flammable. Keep away from heat or flame.
For external use only.
Do not use in or near the eyes. In case of contact, rinse thoroughly with water.
Stop use and ask a doctor if irritation or rash occurs.
Keep out of reach of children. IF swallowed, get medical attention or contact a poison center immediately.

DIRECTIONS
Apply liberally to dry hands, rub briskly until evaporated.
Children should be supervised when using this product

INACTIVE INGREDIENT

INACTIVE INGREDIENTS Aqua, Glycerine, Lemon Oil, Zingiber Officinale (Ginger) Oil, Citrus Paradisi (Grapefruit) Oil, Cedarwood Oil, Sandalwood Oil, Lavandula (Lavender) Oil, Fragrance

DIRECTIONS
Apply liberally to dry hands, rub briskly until evaporated.
Children should be supervised when using this product

WARNINGS
Flammable. Keep away from heat or flame.
For external use only.
Do not use in or near the eyes. In case of contact, rinse thoroughly with water.
Stop use and ask a doctor if irritation or rash occurs.
Keep out of reach of children. IF swallowed, get medical attention or contact a poison center immediately.

USE
Hand sanitizer to help reduce disease-causing bacteria.

PACKAGE LABEL

AMASS

PSEUDO CITRINE

LEMON

GINGER

GRAPEFRUIT

LAVENDER

70% Alcohol-based hand sanitizer for when water is not available. Manufactured in Los Angeles, California.

2 oz | 59 mL

-------------------------- Premium Botanics